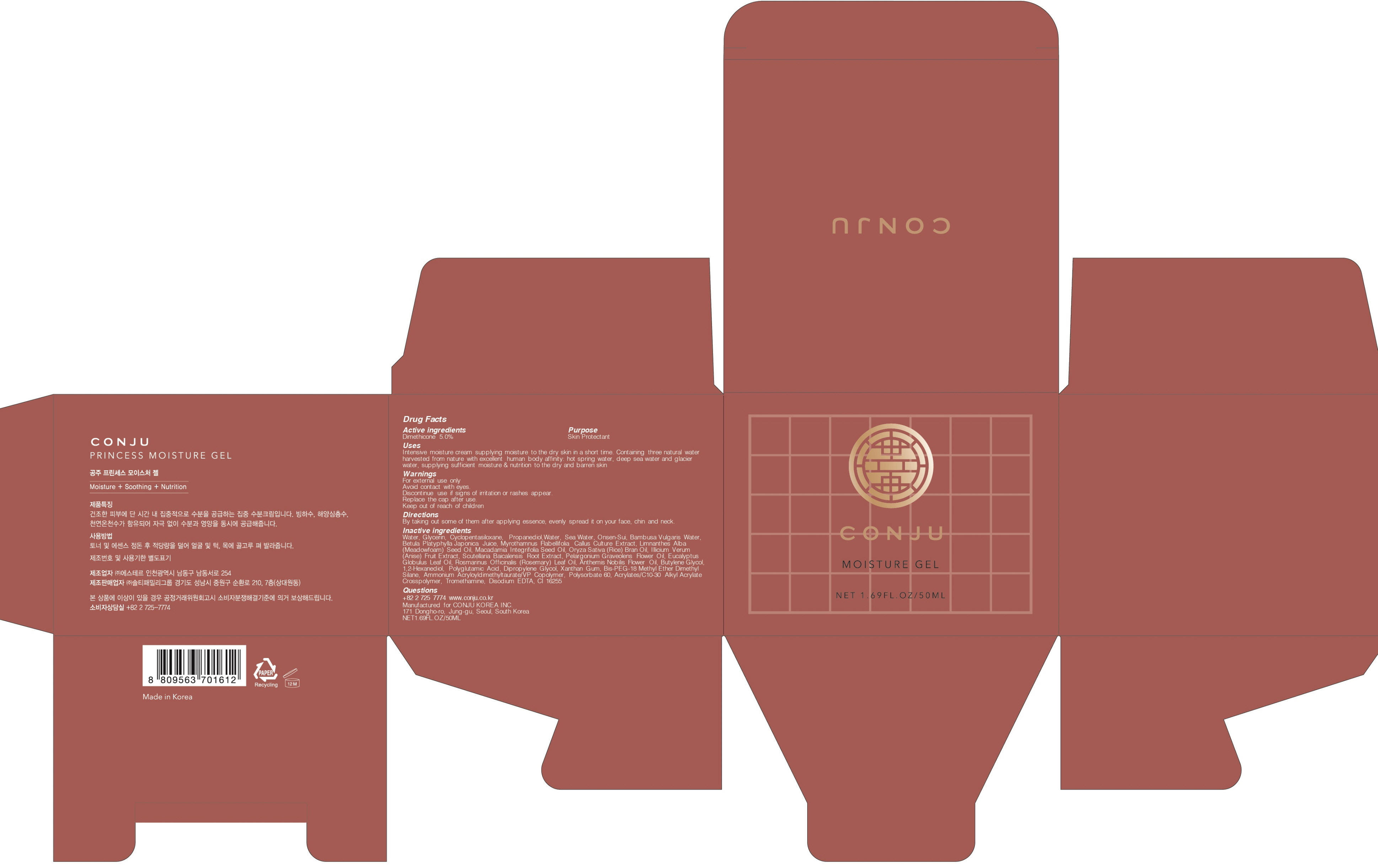 DRUG LABEL: CONJU PRINCESS MOISTURE
NDC: 72950-050 | Form: GEL
Manufacturer: Conju Korea Inc.
Category: otc | Type: HUMAN OTC DRUG LABEL
Date: 20190318

ACTIVE INGREDIENTS: Dimethicone 2.5 g/50 mL
INACTIVE INGREDIENTS: Water; Glycerin

ACTIVE INGREDIENT

Active ingredient: Dimethicone 5.0%

INACTIVE INGREDIENT

Inactive ingredients:

Water, Glycerin, Cyclopentasiloxane, Propanediol,Water, Sea Water, Onsen-Sui, Bambusa Vulgaris Water, Betula Platyphylla Japonica Juice, Myrothamnus Flabellifolia Callus Culture Extract, Limnanthes Alba (Meadowfoam) Seed Oil, Macadamia Integrifolia Seed Oil, Oryza Sativa (Rice) Bran Oil, Illicium Verum (Anise) Fruit Extract, Scutellaria Baicalensis Root Extract, Pelargonium Graveolens Flower Oil, Eucalyptus Globulus Leaf Oil, Rosmarinus Officinalis (Rosemary) Leaf Oil, Anthemis Nobilis Flower Oil, Butylene Glycol, 1,2-Hexanediol, Polyglutamic Acid, Dipropylene Glycol, Xanthan Gum, Bis-PEG-18 Methyl Ether Dimethyl Silane, Ammonium Acryloyldimethyltaurate/VP Copolymer, Polysorbate 60, Acrylates/C10-30 Alkyl Acrylate Crosspolymer, Tromethamine, Disodium EDTA, CI 16255

PURPOSE

Purpose: Skin Protectant

WARNINGS

For external use only
Avoid contact with eyes.
Discontinue use if signs of irritation or rashes appear.
Replace the cap after use.
Keep out of reach of children

KEEP OUT OF REACH OF CHILDREN

Uses

Intensive moisture cream supplying moisture to the dry skin in a short time. Containing three natural water harvested from nature with excellent human body affinity: hot spring water, deep sea water and glacier water, supplying sufficient moisture & nutrition to the dry and barren skin

Directions

By taking out some of them after applying essence, evenly spread it on your face, chin and neck.